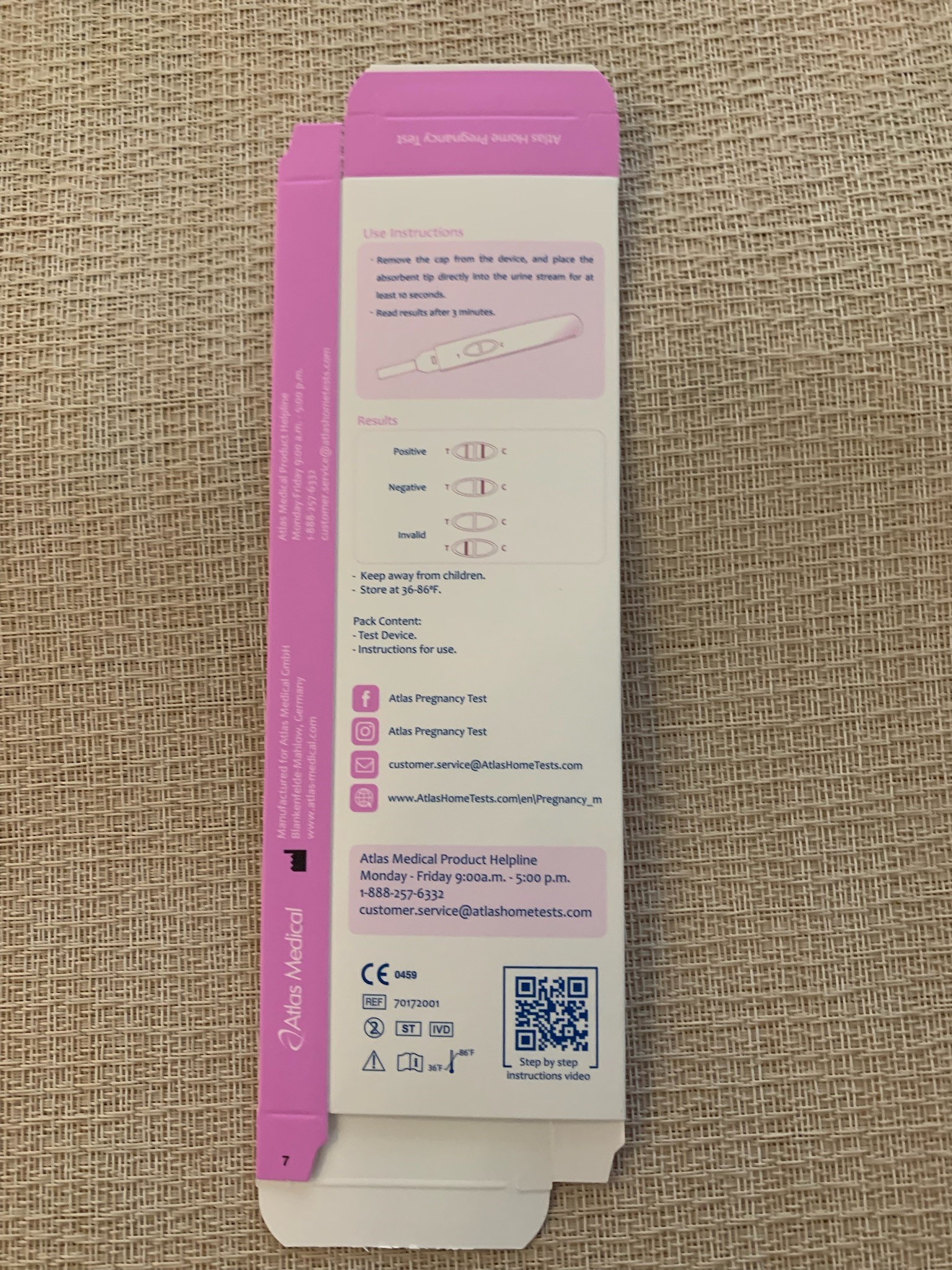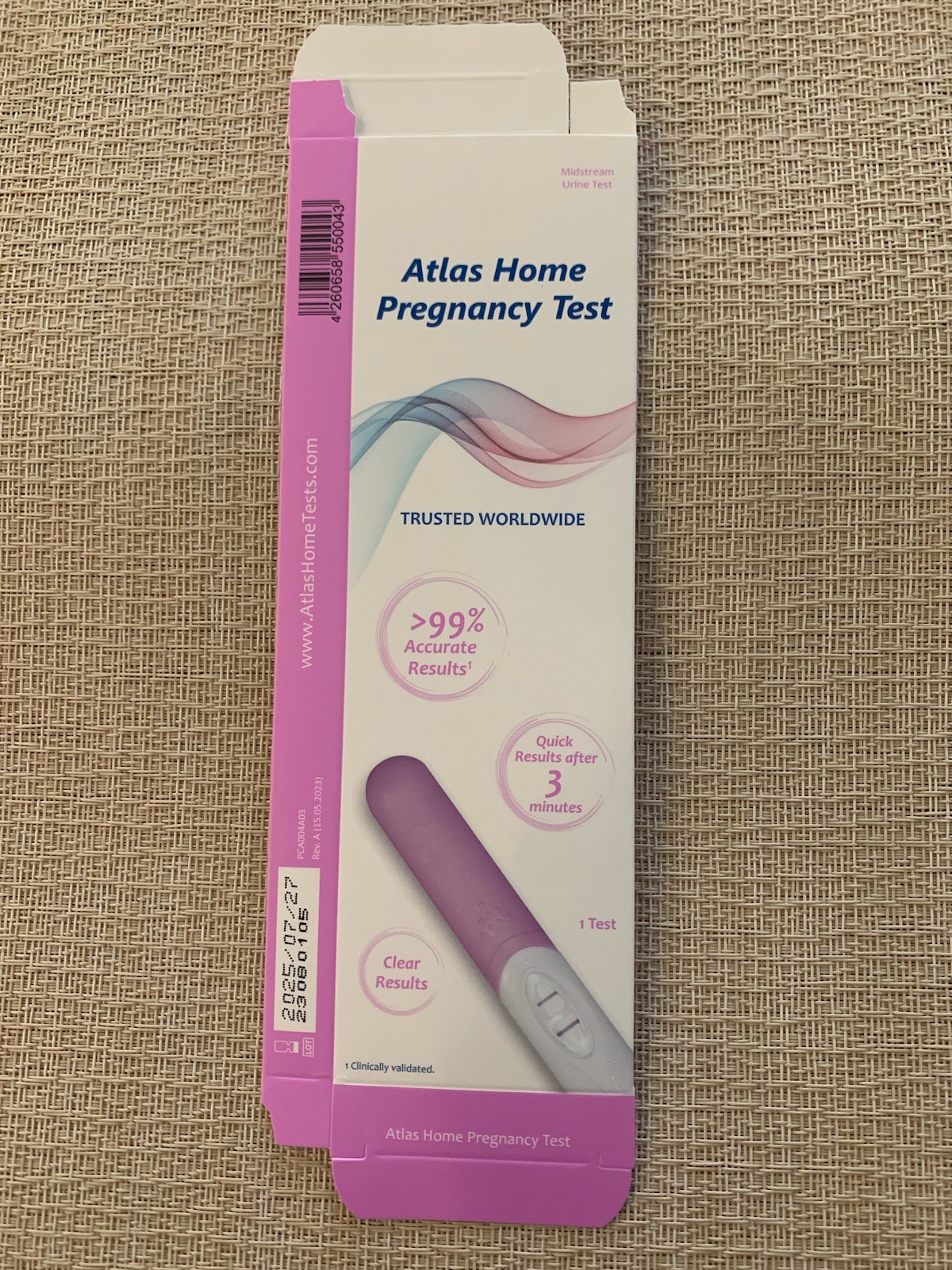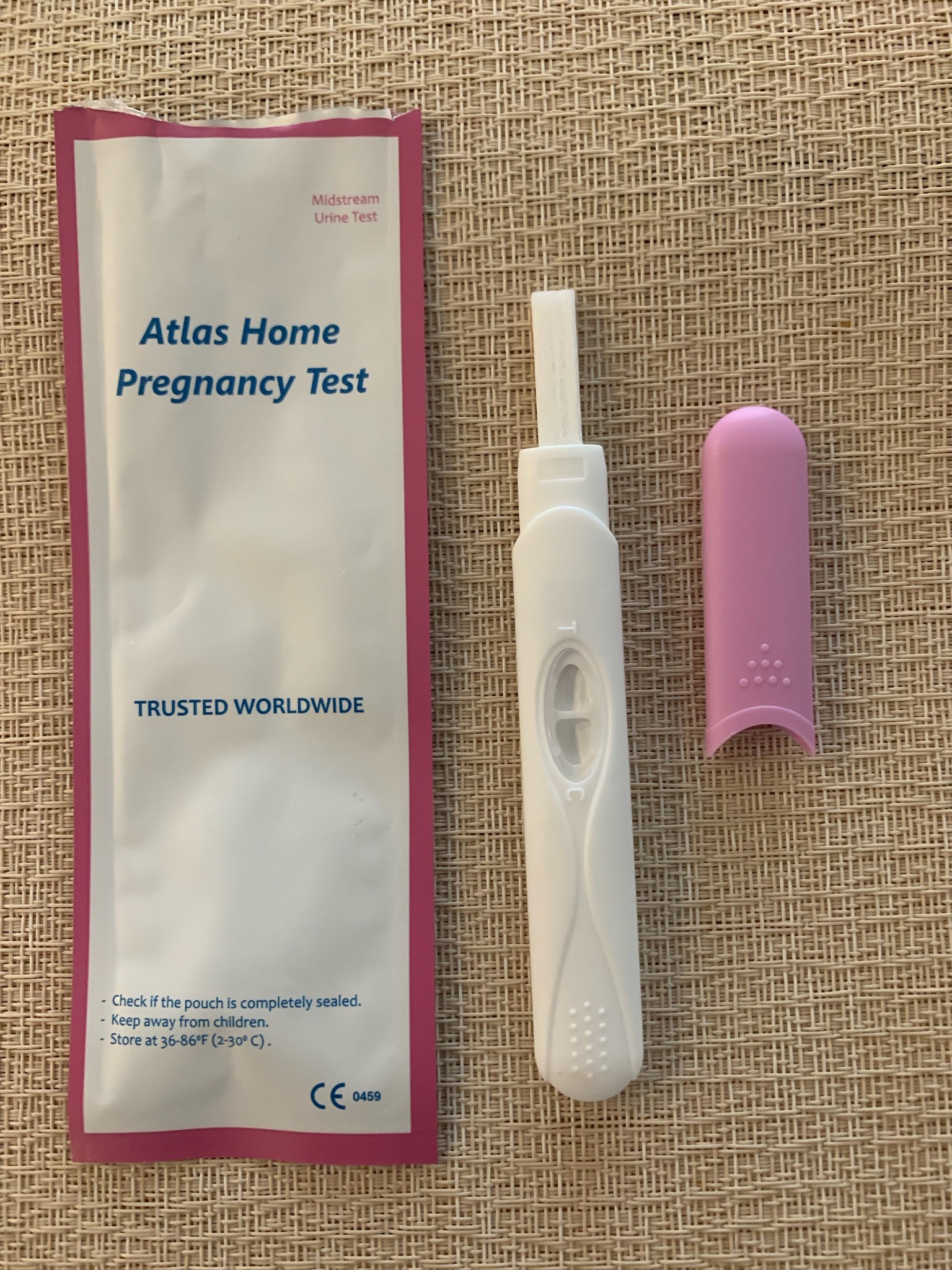 DRUG LABEL: Atlas Pregnancy Test
NDC: 77468-200
Manufacturer: ECLIPSE PHARMA LLC
Category: other | Type: PRESCRIPTION MEDICAL DEVICE LABEL
Date: 20231108

Atlas Pregnancy Test

WARNINGS

- Check if the pouch is completely sealed.
- Keep away from children.
- Store at 36-86℉
- Preg Product

Product Packaging